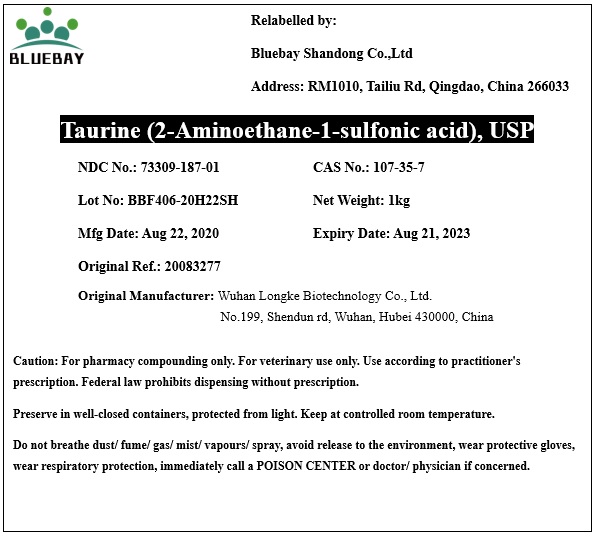 DRUG LABEL: Taurine  (2-Aminoethane-1-sulfonic acid)
NDC: 73309-187 | Form: POWDER
Manufacturer: BLUEBAY SHANDONG CO.,LTD
Category: other | Type: BULK INGREDIENT
Date: 20200908

ACTIVE INGREDIENTS: TAURINE 1 kg/1 kg

Taurine (2-Aminoethane-1-sulfonic acid)